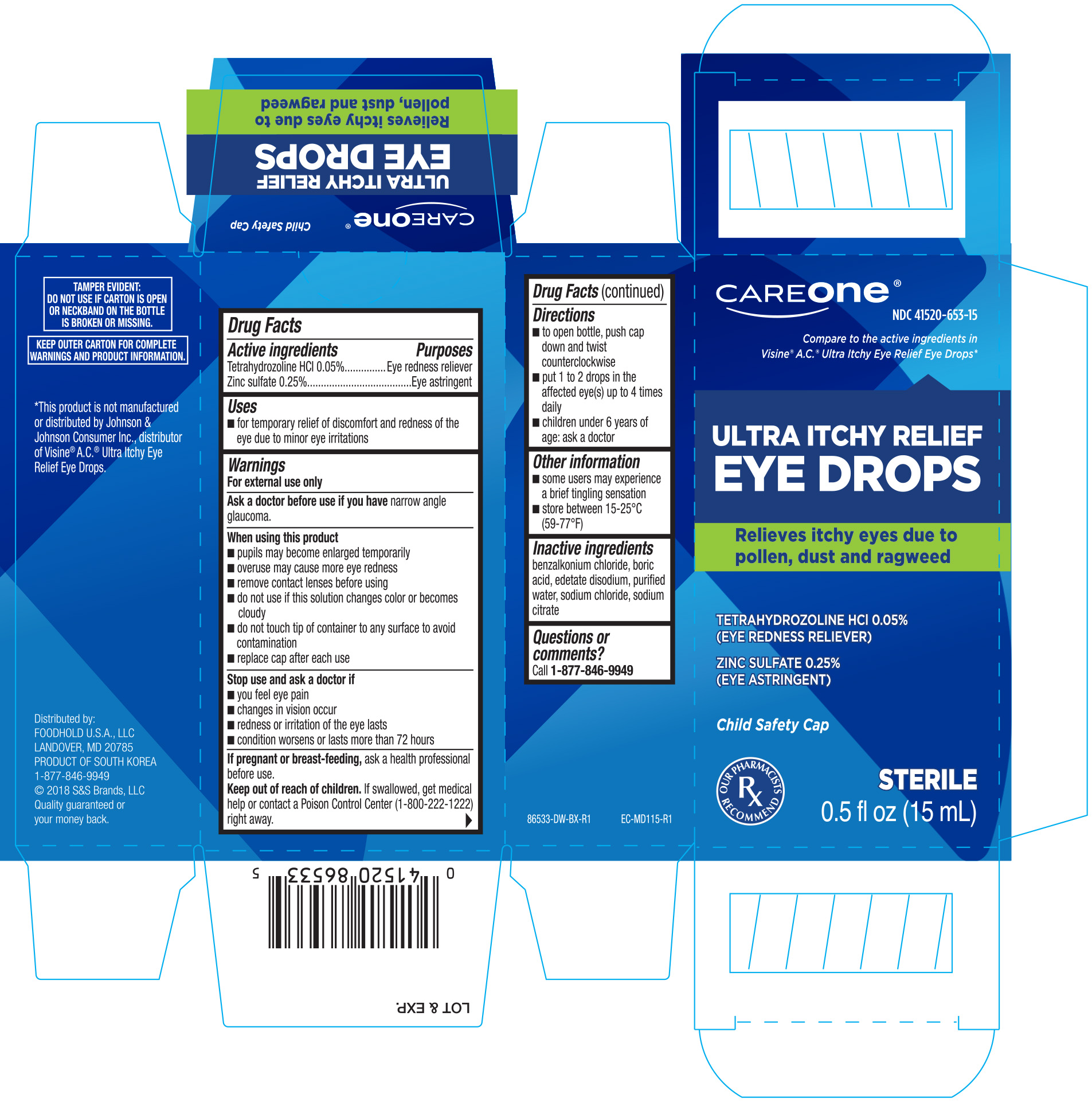 DRUG LABEL: Careone Eye Drops Seasonal Relief
NDC: 41520-653 | Form: SOLUTION/ DROPS
Manufacturer: FoodHold U.S.A LLC
Category: otc | Type: HUMAN OTC DRUG LABEL
Date: 20190501

ACTIVE INGREDIENTS: TETRAHYDROZOLINE HYDROCHLORIDE 0.5 mg/1 mL; ZINC SULFATE 2.5 mg/1 mL
INACTIVE INGREDIENTS: EDETATE DISODIUM; BENZALKONIUM CHLORIDE; BORIC ACID; WATER; SODIUM CHLORIDE; SODIUM CITRATE

Careone Eye Drops Seasonal Relief 0.5 oz (NBE Visine AC) 86533 2018

Active Ingredients Purposes

Tetrahydrozoline HCl 0.05%.......Eye redness reliever

Zinc sulfate 0.25%......................Eye astringent

Uses

- for temporary relief of discomfort and redness of the eye due to minor eye irritations

WARNINGS

For external use only

Ask a doctor before use if you have narrow angle glaucoma.

When using this product

- pupils may become enlarged temporarily
- overuse may cause more eye redness
- remove contact lenses before using
- do not use if this solution changes color or becomes cloudy
- do not touch tip of container to any surface to avoid contamination
- replace cap after each use

Stop use and ask a doctor if

- you feel eye pain
- changes in vision occur
- redness or irritation of the eye lasts
- condition worsens or lasts more than 72 hours

PREGNANCY OR BREAST FEEDING

If pregnant or breast-feeding, ask a health professional before use.

Keep out of reach of children. If swallowed, get medical help or contact a Poison Control Center (1-800-222-1222) right away.

Directions

- to open bottle, push cap down and twist counterclockwise
- put 1 to 2 drops in the affected eye(s) up to 4 times daily
- children under 6 years of age: ask a doctor

STORAGE AND HANDLING

- some users may exprience a brief tingling sensation
- store between 15-25ºC (59-77ºF)

INACTIVE INGREDIENT

benzalkonium chloride, boric acid, edetate disodium, purified water, sodium chloride, sodium citrate

Questions or comments?

Call 1-877-846-9949

DOSAGE AND ADMINISTRATION

Distributed by:

FOODHOLD U.S.A., LLC

LANDOVER, MD 20785

1-877-846-9949